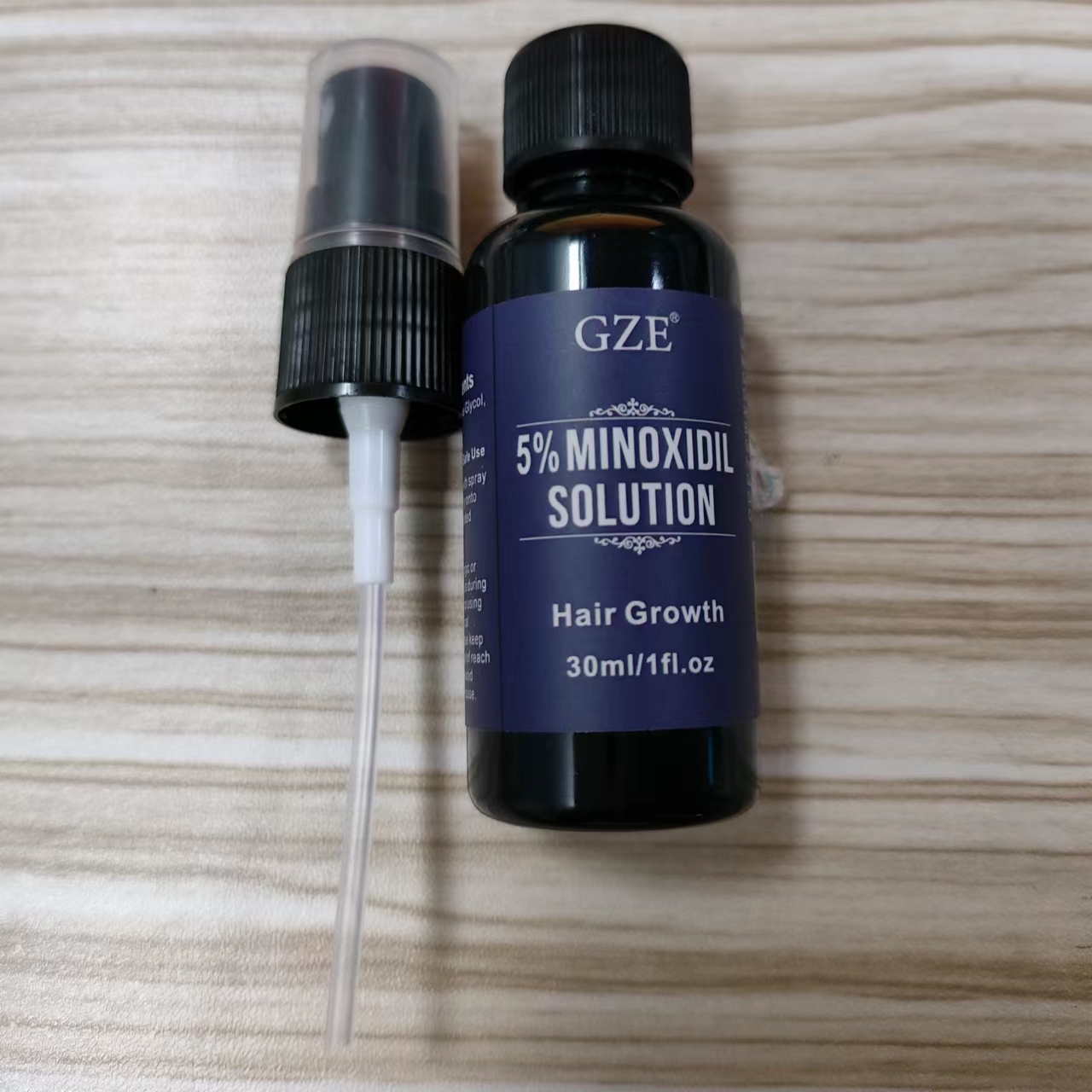 DRUG LABEL: GZE 5% Minoxidil Solution
NDC: 74458-270 | Form: SPRAY
Manufacturer: Guangzhou Yilong Cosmetics Co., Ltd
Category: otc | Type: HUMAN OTC DRUG LABEL
Date: 20241010

ACTIVE INGREDIENTS: MINOXIDIL 5 g/100 mL
INACTIVE INGREDIENTS: WATER; PROPYLENE GLYCOL

GZE 5% MINOXIDIL SOLUTION

ACTIVE INGREDIENT

Minoxidil

INACTIVE INGREDIENT

Aqua, Propylene Glycol

INDICATIONS AND USAGE

Apply one mL with spray 2X a day directly onto scalp in the needed area.

PURPOSE

Hair growth.

WARNINGS

For external use only.

Stop use and ask a doctor if rash occurs.

Do not use on damaged or broken skin.

When using this product keep out of eyes. Rinse with water to remove.

Keep out of reach of children. If swallowed, get medical help or contact a Poison Control Center right away.

DOSAGE AND ADMINISTRATION

Apply one mL with spray 2X a day directly onto scalp in the needed area.